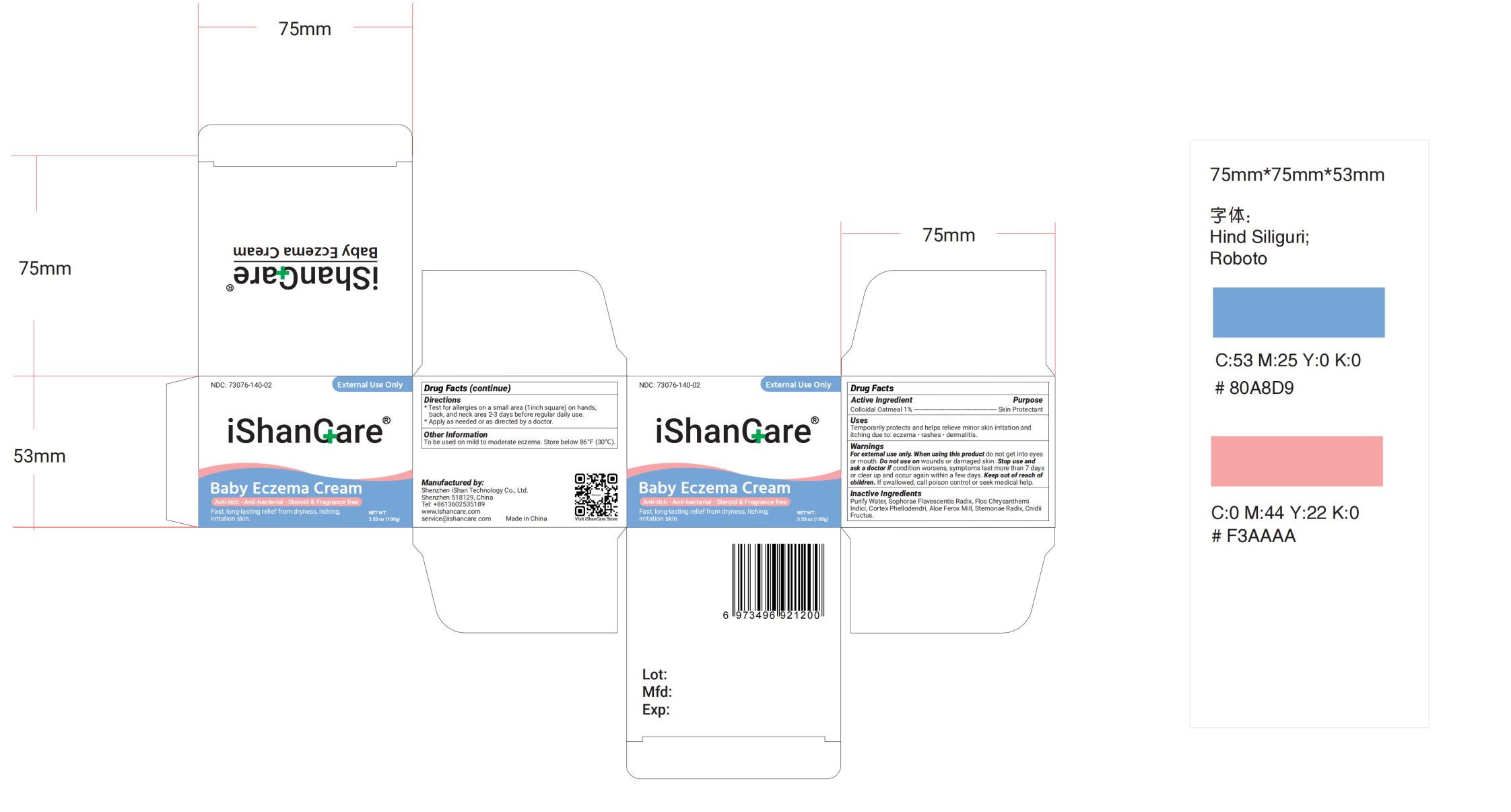 DRUG LABEL: iShancare Baby Eczema Cream
NDC: 73076-152 | Form: CREAM
Manufacturer: Shenzhen Ishan Technology Co., Ltd
Category: homeopathic | Type: HUMAN OTC DRUG LABEL
Date: 20260213

ACTIVE INGREDIENTS: OATMEAL 1 g/100 g
INACTIVE INGREDIENTS: CNIDIUM MONNIERI FRUIT 3 g/100 g; STEMONA JAPONICA ROOT 0.5 g/100 g; PHELLODENDRON CHINENSIS BARK; CHRYSANTHEMIN 2 g/100 g; ALOE FEROX LEAF 0.5 g/100 g; SOPHORA FLAVESCENS ROOT 1.5 g/100 g; WATER

Directions

* Test for allergies on a small area (1inch square) on hands,
back, and neck area 2-3 days before regular daily use.
* Apply as needed or as directed by a doctor.

Active Ingredient

Colloidal Oatmeal 1% ---------------------------------------------- Skin Protectant

Ask doctor

Stop using and ask a doctor if condition worsens, symptoms last more than 7 days or clear up and occur again within a few days.

Do not use on wounds or damaged skin.

Keep out of reach of children. If swallowed, call poison control or seek medical help.

Stop use and ask a doctor if condition worsens, symptoms last more than 7 days or clear up and occur again within a few days.

When using this product do not get into eyes or mouth.

WARNINGS

For external use only. When using this product
do not get into eyes or
mouth. Stop use and ask a doctor if condition worsens, symptoms last
more than 7 days or clear up and occur again within a few days.
Do not use
on deep puncture wounds, serious burns. Keep out of reach of children. If
swallowed, call poison control or seek medical help.

INACTIVE INGREDIENT

Purify Water, Cnidium Seed, Phellodendron Chinensis Bark, Chrysanthemin, Sophora Flavescens Root, Stemona Japonica Root, Aloe Ferox Leaf, Menthol.

INDICATIONS AND USAGE

* Try on a small patch of skin first to be sure your child does not react.
* Wash and dry affected area, apply a thin layer of LMNOOP over affected
area, gently massage until fully absorbed, repeat 2-3 times daily.

PURPOSE

Temporarily protects and helps relieve minor skin irritation and itching due
to eczema, rashes, dermatitis.